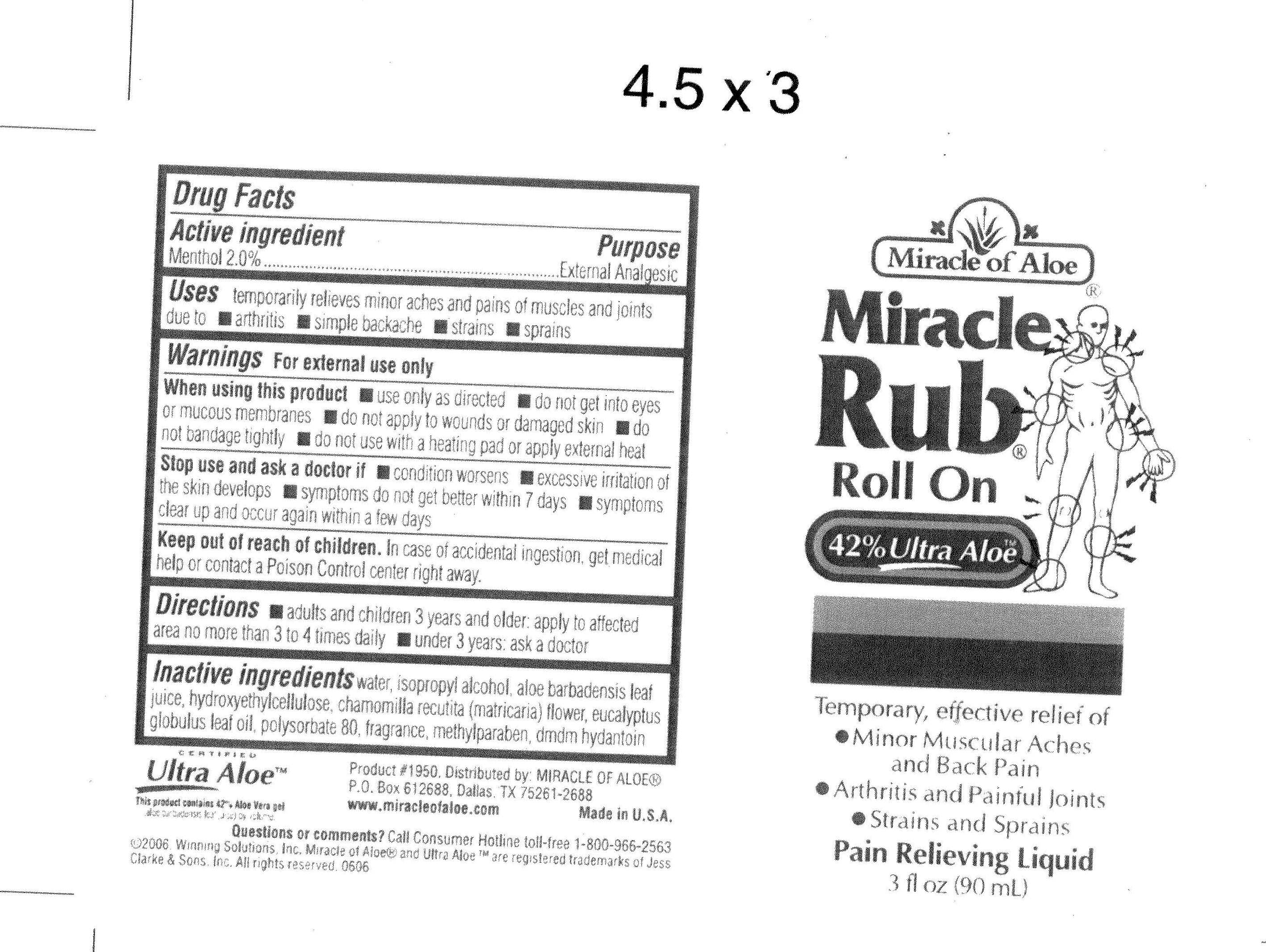 DRUG LABEL: Miracle of Aloe Rub Roll On
NDC: 66391-0046 | Form: LIQUID
Manufacturer: Winning Solutions
Category: otc | Type: HUMAN OTC DRUG LABEL
Date: 20110404

ACTIVE INGREDIENTS: Menthol 1.8 mL/90 mL
INACTIVE INGREDIENTS: Water; ISOPROPYL ALCOHOL; ALOE VERA LEAF; HYDROXYETHYL CELLULOSE (140 CPS AT 5%); CHAMOMILE; CORYMBIA CITRIODORA LEAF OIL; polysorbate 80; methylparaben; dmdm hydantoin

Active Ingredient : Menthol 2.0 %

Purpose : External Analgesic

Warnings : For external use only

Keep Out of Reach of Children : In case of accidental ingestion , get medical help or contact a Position Control center right away.

DOSAGE AND ADMINISTRATION

Directions : adults and children 3 years and older ; apply to affected area no more than 3 to 4 times daily
under 3 years: ask a doctor

INACTIVE INGREDIENT

Inactive Ingredients : water , isopropyl alcohol , aloe barbadensis leaf juice , hydroxyethylcellulose , chamomilla recutita (matricaria) flower , eucalyptus globulus leaf oil , polysorbate 80 , fragrance , methylparaben , dmdm hydantoin

INDICATIONS AND USAGE

Uses : Temporarily relieves minor aches and pains of muscles and joints due to * arthritis * simple backache * strains * sprains